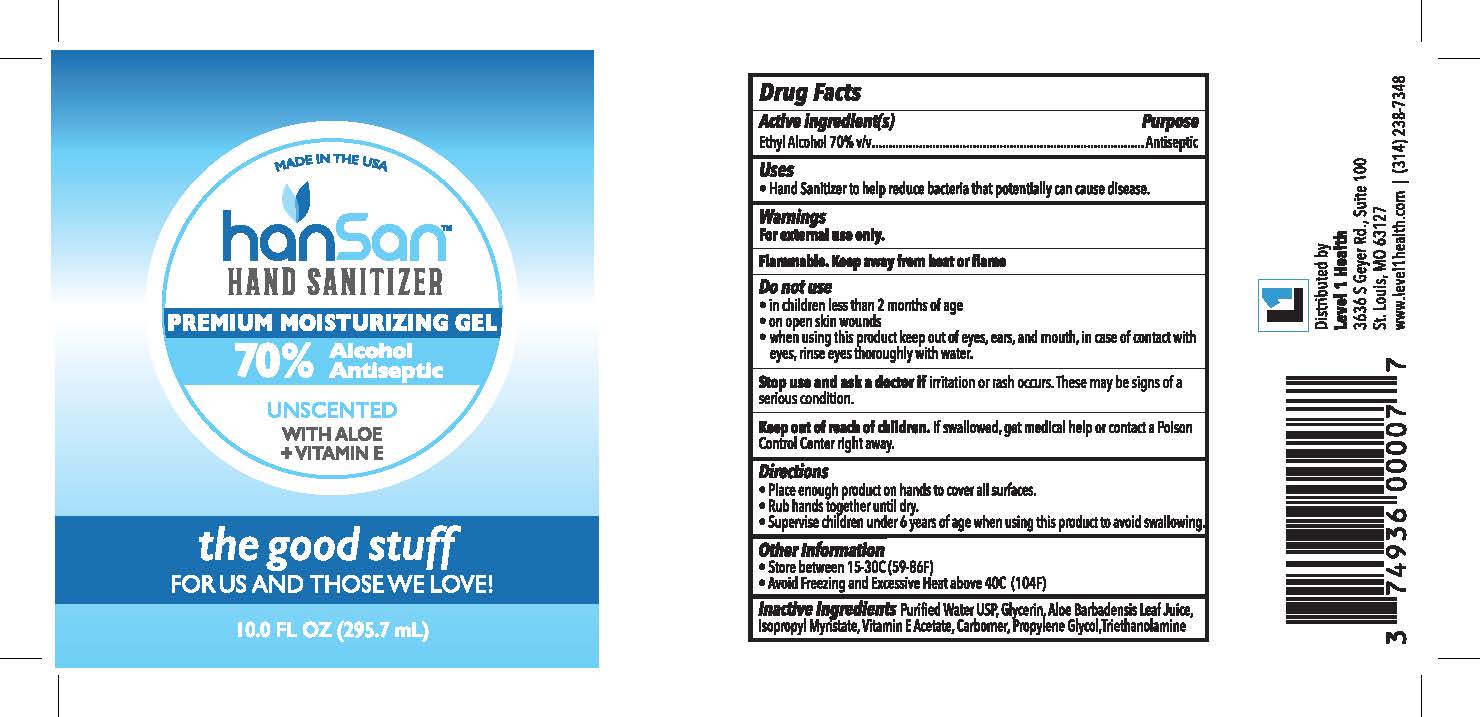 DRUG LABEL: HanSan Hand Sanitizer
NDC: 74936-002 | Form: GEL
Manufacturer: Level 1 Health LLC
Category: otc | Type: HUMAN OTC DRUG LABEL
Date: 20200622

ACTIVE INGREDIENTS: ALCOHOL 70 mL/100 mL
INACTIVE INGREDIENTS: TROLAMINE; GLYCERIN; ALOE VERA LEAF; WATER; ISOPROPYL MYRISTATE; .ALPHA.-TOCOPHEROL ACETATE, DL-; CARBOMER INTERPOLYMER TYPE A (55000 CPS); PEG-40 CASTOR OIL

HanSan Hand Sanitizer

Active Ingredient(s)

Ethyl Alcohol 70% v/v

Purpose

Antiseptic

Use

Hand Sanitizer to help reduce bacteria that potentially can cause disease.

Warnings

For external use only. Flammable. Keep away from heat or flame

Do not use

- in children less than 2 months of age
- on open skin wounds

When using this product keep out of eyes, ears, and mouth, in case of contact with eyes, rinse eyes thoroughly with water.

Stop use and ask a doctor if irritation or rash occurs. These may be signs of a serious condition.

Keep out of reach of children. If swallowed, get medical help or contact a Poison Control Center right away.

Directions

- Place enough product on hands to cover all surfaces.
- Rub hands together until dry.
- Supervise children under 6 years of age when using this product to avoid swallowing.

Other information

- Store between 15-30C (59-86F)
- Avoid freezing and excessive heat above 40C (104F)

Inactive ingredients

Purified water USP, Glycerin, Aloe Barbadensis Leaf Juice, Isopropyl Myristate, Vitamine E Acetate, Carbomer, Propylene Glycol, Triethanolamine

Package Label - Principal Display Panel

HanSan (tm) Hand Sanitizer

Premium Moisturizing Gel

70% Alcohol Antiseptic

Unscented

WITH ALOE + VITAMIN E

the good stuff

For Us and Those We Love!

XX FL OZ (XXX.X mL)

MADE IN USA

Distributed by

Level 1 Health

3636 S Geyer Rd. Suite 100

St. Louis, MO 63127

www.level1health.com | (314) 238-7348

UPC Code